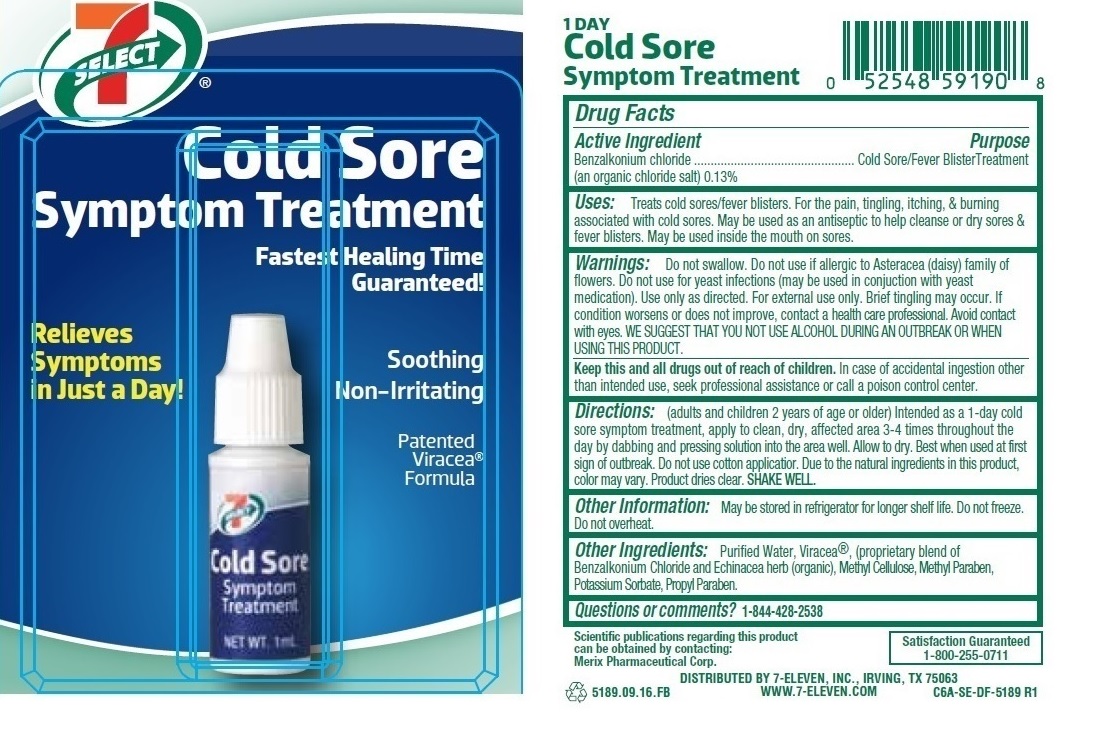 DRUG LABEL: 7 SELECT Cold Sore Symptom Treatment
NDC: 10202-591 | Form: SOLUTION
Manufacturer: 7-eleven
Category: otc | Type: HUMAN OTC DRUG LABEL
Date: 20200102

ACTIVE INGREDIENTS: BENZALKONIUM CHLORIDE 1.3 mg/1 mL
INACTIVE INGREDIENTS: WATER; ECHINACEA PURPUREA FLOWERING TOP; HYPROMELLOSE 2910 (4000 MPA.S); METHYLPARABEN; POTASSIUM SORBATE; PROPYLPARABEN

7 SELECT Cold Sore Symptom Treatment

Active Ingredient

Benzalkonium chloride

(an organic chloride salt) 0.13%

Purpose

Cold Sore/Fever Blister Treatment

INDICATIONS AND USAGE

Uses: Treats cold sores/fever blisters. For the pain, tingling, itching, & burning associated with cold sores. May be used as an antiseptic to help cleanse or dry sores & fever blisters. May be used inside the mouth on sores.

WARNINGS

Warnings: Do not swallow. Do not use if allergic to Asteracea (daisy) family of flowers. Do not use for yeast infections (may be used in conjuction with yeast medication). Use only as directed. For external use only. Brief tingling may occur. If conditions worsens or does not improve, contact a health care professional. Avoid contact with eyes. WE SUGGEST THAT YOU NOT USE ALCOHOL DURING AN OUTBREAK OR WHEN USING THIS PRODUCT.

KEEP OUT OF REACH OF CHILDREN

Keep this and all drugs out of reach of children. In case of accidental ingestion other than intended use, seek professional assistance or call a poison control center.

DOSAGE AND ADMINISTRATION

Directions: (adults and children 2 years of age or older) Intended as a 1-day cold sore symptom treatment, apply to clean, dry, affected area 3-4 times throughout the day by dabbing and pressing solution into the area well. Allow to dry. Best when used at first sign of outbreak. Do not use cotton applicator. Due to the natural ingredients in this product, color may vary. Product dries clear. SHAKE WELL.

INACTIVE INGREDIENT

Other Ingredients: Purified Water, Viracea, (proprietary blend of Benzalkonium Chloride and Echinacea herb (organic), Hypromellose, Methyl Paraben, Potassium Sorbate, Propyl Paraben.

Other Information: May be stored in refrigerator for longer shelf life. Do not freeze. Do not overheat.

Questions or comments?1-844-428-2538

Fastest Healing Time Guaranteed!

Relieves Symptoms in Just a Day!

Soothing

Non-Irritating

Patented Viracea Formula

1 DAY Cold Sore Symptom Treatment

Scientific publications regarding this product can be obtained by contacting:

Merix Pharmaceutical Corp.

Satisfaction Guaranteed

1-800-255-0711